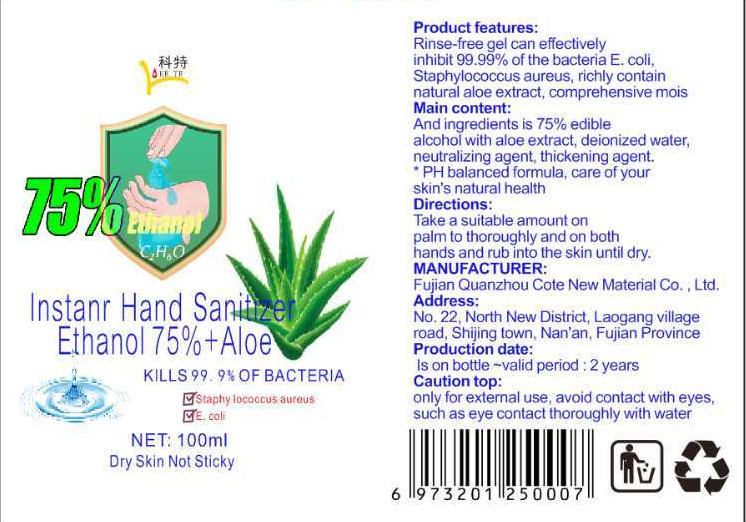 DRUG LABEL: 75 alcohol hand sanitizer
NDC: 41562-001 | Form: LIQUID
Manufacturer: Fujian Quanzhou Kete New Material Co., Ltd.
Category: otc | Type: HUMAN OTC DRUG LABEL
Date: 20200426

ACTIVE INGREDIENTS: ALOE 1 mg/100 mL; ALCOHOL 75 mL/100 mL
INACTIVE INGREDIENTS: WATER

DOSAGE AND ADMINISTRATION

Sealed in dark.

INACTIVE INGREDIENT

Water

INDICATIONS AND USAGE

Take a suitable amount on npalm to thoroughly and on both hands and rub into the skin until dry.

ACTIVE INGREDIENT

alcohol

Aloe Gel

keep out of children

PURPOSE

Disinfection
Sterilization

WARNINGS

only for extermal use, avoid contact with eyes,such as eye contact thoroughly with water